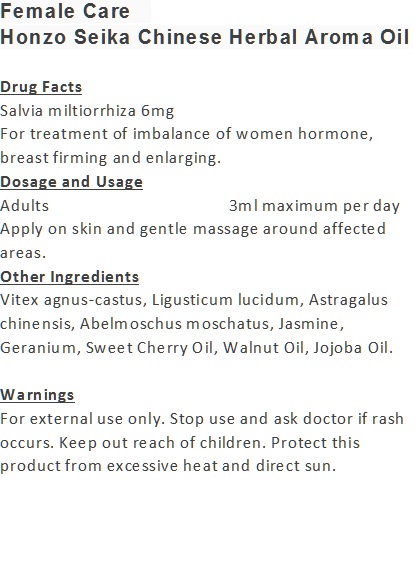 DRUG LABEL: Female Care
NDC: 70470-9912 | Form: OIL
Manufacturer: Phytopia Co., Ltd.
Category: otc | Type: HUMAN OTC DRUG LABEL
Date: 20170101

ACTIVE INGREDIENTS: SALVIA MILTIORRHIZA ROOT 6 mg/100 mL
INACTIVE INGREDIENTS: LIGUSTRUM LUCIDUM WHOLE; SWEET CHERRY SEED OIL; WALNUT OIL; JOJOBA OIL; VITEX AGNUS-CASTUS WHOLE; ASTRAGALUS CHINENSIS SEED; GERANIUM OIL, ALGERIAN TYPE; ABELMOSCHUS MOSCHATUS SEED; JASMINUM OFFICINALE FLOWER

Drug Facts

Salvia miltiorrhiza 6mg

Use

For treatment of imbalance of women hormone, breast firming and enlarging.

Dosage Suggestion

Adults 3ml maximum per day

INACTIVE INGREDIENT

Other Ingredients

Vitex agnus-castus, Ligusticum lucidum, Astragalus chinensis, Abelmoschus moschatus, Jasmine, Geranium, Sweet Cherry Oil, Walnut Oil, Jojoba Oil.

Directions

Apply on skin and gentle massage around affected area.

Warnings

For external use only. Stop use and ask doctor if rash occurs. Keep out reach of children.

Other Information

Protect this product from excessive heat

and direct sun.

Warnings

For external use only. Stop use and ask doctor if rash occurs. Keep out reach of children.